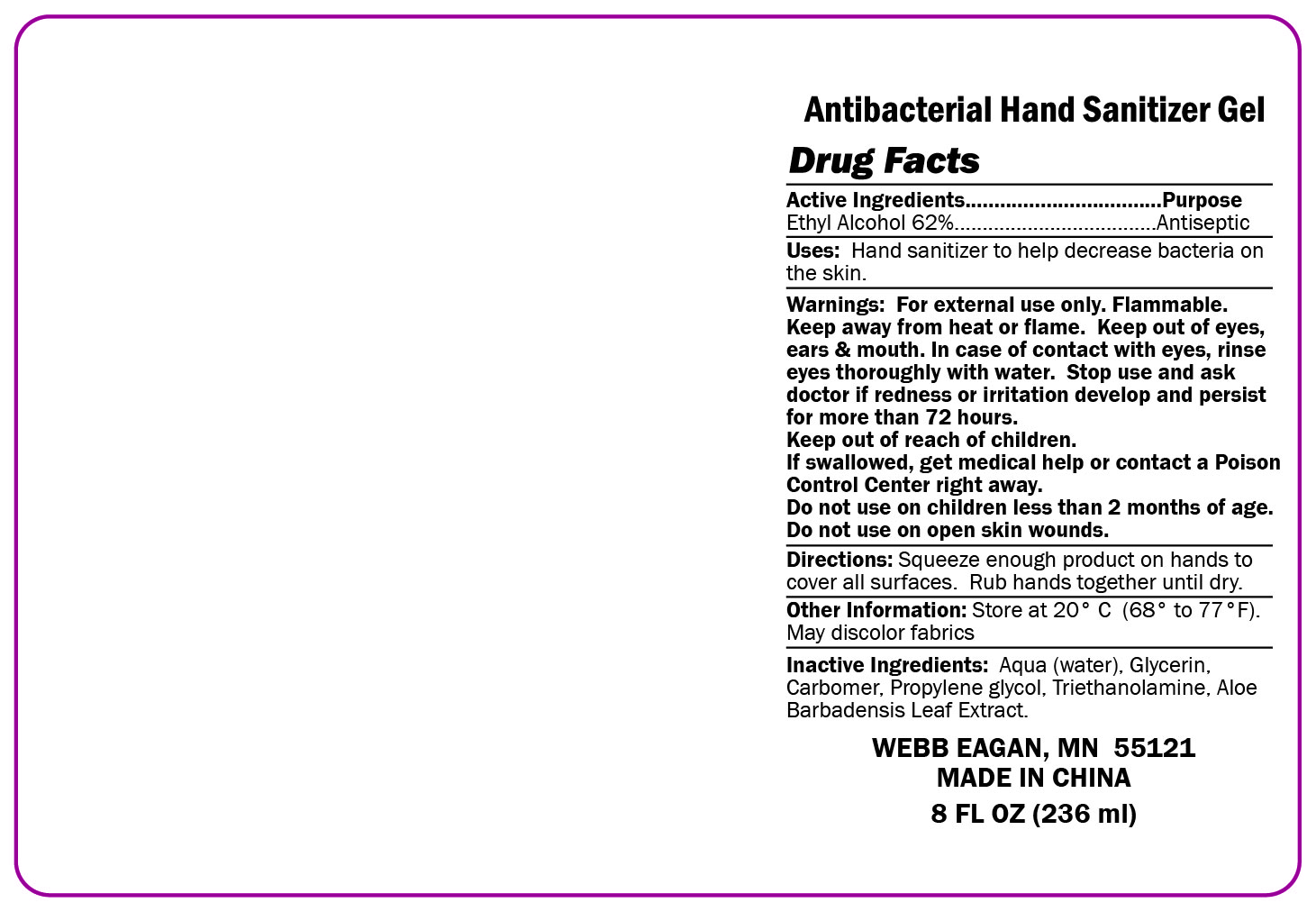 DRUG LABEL: Antibacterial Hand Sanitizer
NDC: 70445-416 | Form: GEL
Manufacturer: Webb Business Promotions, Inc
Category: otc | Type: HUMAN OTC DRUG LABEL
Date: 20220104

ACTIVE INGREDIENTS: ALCOHOL 62 mL/100 mL
INACTIVE INGREDIENTS: ALOE VERA LEAF; CARBOMER 940; TROLAMINE; WATER; PROPYLENE GLYCOL; GLYCERIN

Antibacterial Hand Sanitizer

Warnings

For external use only. Flammable

Do not use on children less than 2 month of age. Do not use on open skin wounds.

Stop use and ask doctor if redeness or irritation develop and persist for more than 72 hours

Stop use and ask doctor if redenss or irritation develop and persist for more than 72 hours

Keep out of reach of children

STORAGE AND HANDLING

Store at 20 C (68-77 F). May discolore fabrics

Purpose

Antiseptic

Directions

Squeeze enough product on hands to cover all surfaces. Rub hands together untill dry.

OTHER SAFETY INFORMATION

Keep away from heat and flame. Keep out of eyes, ears, and mouth.

INDICATIONS AND USAGE

Squezze enough product on hands to cover all surfaces. Rub hands together untill dry.

Active Ingridient

Ethyl Alcohol 62%

Inactive Ingridient section

Trolamine. Water. Propylene Glycol. Aloe Vera. Carbomer. Glycerine.